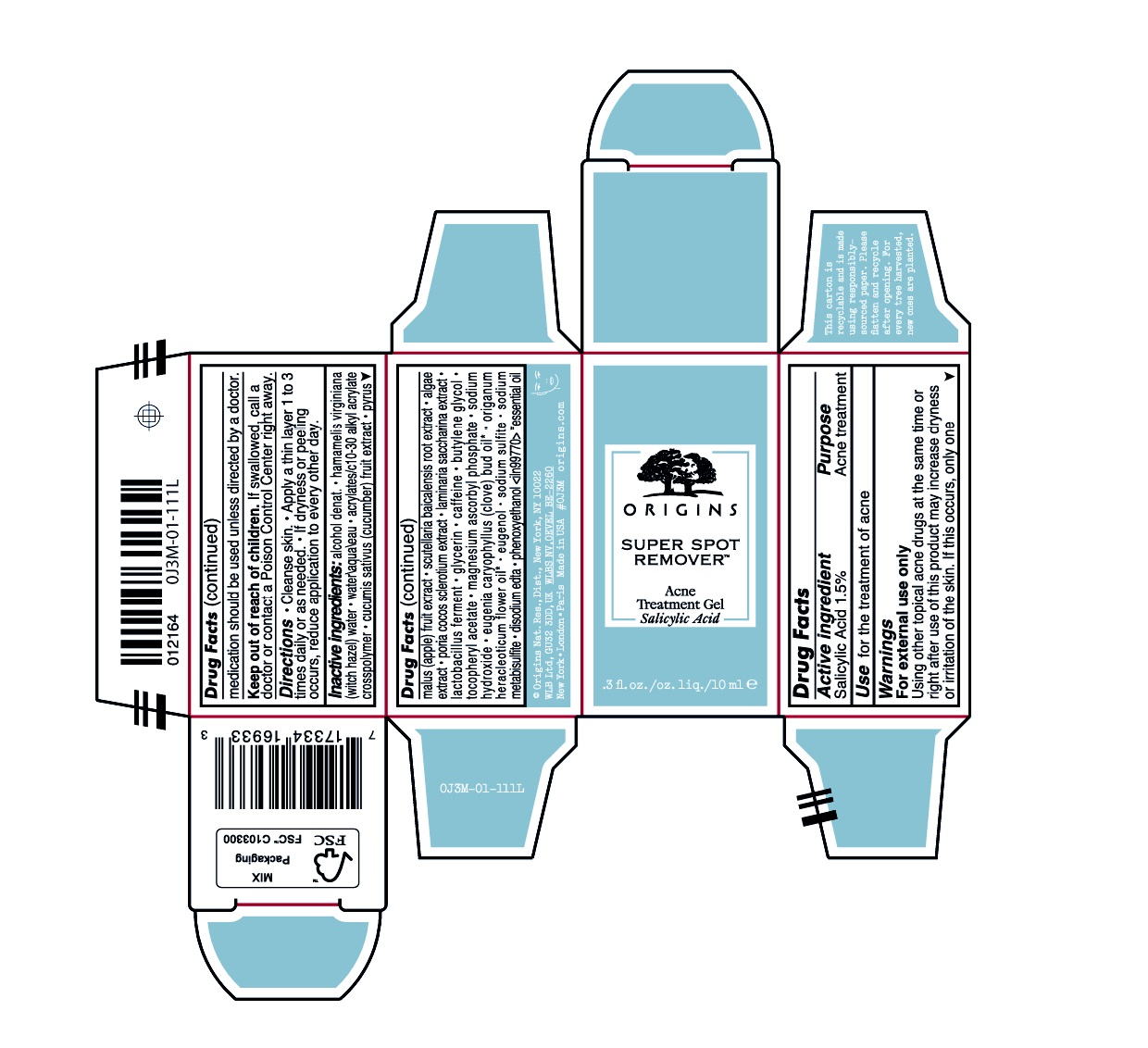 DRUG LABEL: SUPER SPOT REMOVER ACNE TREATMENT
NDC: 59427-005 | Form: GEL
Manufacturer: ORIGINS NATURAL RESOURCES INC.
Category: otc | Type: HUMAN OTC DRUG LABEL
Date: 20251215

ACTIVE INGREDIENTS: SALICYLIC ACID 15 mg/1 mL
INACTIVE INGREDIENTS: SODIUM SULFITE; SODIUM METABISULFITE; EDETATE DISODIUM ANHYDROUS; HAMAMELIS VIRGINIANA TOP WATER; ORIGANUM VULGARE SUBSP. HIRTUM FLOWER; WATER; CLOVE OIL; EUGENOL; CUCUMBER; APPLE; SCUTELLARIA BAICALENSIS ROOT; SACCHARINA LATISSIMA; GLYCERIN; CAFFEINE; BUTYLENE GLYCOL; .ALPHA.-TOCOPHEROL ACETATE; MAGNESIUM ASCORBYL PHOSPHATE; SODIUM HYDROXIDE; PHENOXYETHANOL; FU LING; LIMOSILACTOBACILLUS FERMENTUM; PORPHYRIDIUM PURPUREUM; ALCOHOL; ACRYLATES/C10-30 ALKYL ACRYLATE CROSSPOLYMER (60000 MPA.S)

SUPER SPOT REMOVER™ ACNE TREATMENT

Active ingredient

Salicylic Acid 1.5%

Purpose

Acne treatment

Uses

- for the management of acne
- clears acne blemishes
- helps prevent development of new acne blemishes

Warnings

For external use only.

Keep out of reach of children.If swallowed, call a doctor or contact a Poison Control Center right away.

When using this product

skin irritation and dryness is more likely to occur if you use another topical medication at the same time. If this occurs, only use one toptical acne medication at the same time. If this occurs, only use one topical acne medication at a time.

Directions

- Cleanse skin thoroughly before applying
- cover the entire affected area with a thin layer one to three times daily
- because excessive drying of the skin may occur, start with one application daily, then gradually increase to two or three times daily if needed or as directed by a doctor
- if bothersome dryness or peeling occurs, reduce application to once a day or every other day

Inactive ingredients

alcohol denat.,hamamelis virginiana (witch hazel) water,water\aqua\eau,acrylates/c10-30 alkyl acrylate crosspolymer,cucumis sativus (cucumber) fruit extract,pyrus malus (apple) fruit extract,scutellaria baicalensis root extract,algae extract,poria cocos sclerotium extract,laminaria saccharina extract,lactobacillus ferment,glycerin,caffeine,butylene glycol,tocopheryl acetate,magnesium ascorbyl phosphate,sodium hydroxide,eugenia caryophyllus (clove) bud oil1,origanum heracleoticum flower oil1,eugenol,sodium sulfite,sodium metabisulfite,disodium edta,phenoxyethanol

PACKAGE LABEL

ORIGINS

Super Spot
Remover ™

Acne treatment gel
salicylic acid 1.5%

.3 fl. oz./oz. liq./10 ml e